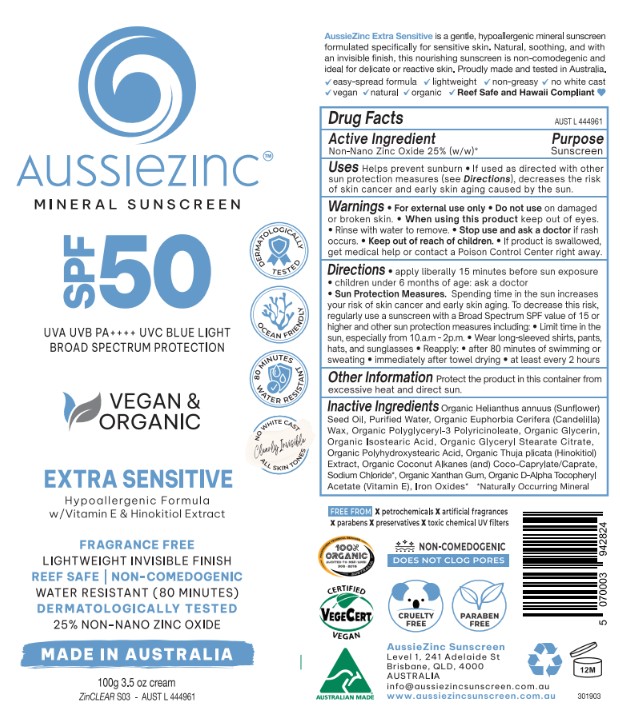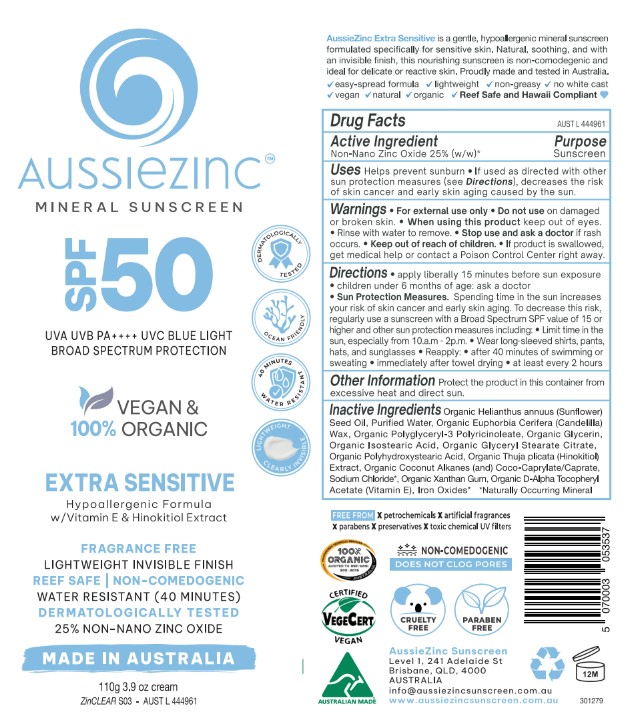 DRUG LABEL: AussieZinc Mineral Sunscreen Vegan and Organic Extra Sensitive
NDC: 83252-100 | Form: CREAM
Manufacturer: VEGANIC SKN LIMITED
Category: otc | Type: HUMAN OTC DRUG LABEL
Date: 20251023

ACTIVE INGREDIENTS: ZINC OXIDE 25 kg/100 kg
INACTIVE INGREDIENTS: COCONUT ALKANES; HELIANTHUS ANNUUS (SUNFLOWER) SEED OIL; TOCOPHEROL; WATER; POLYHYDROXYSTEARIC ACID (2300 MW); ISOSTEARIC ACID; CANDELILLA WAX; SODIUM CHLORIDE; GLYCERIN; POLYGLYCERYL-3 RICINOLEATE; FERRIC OXIDE YELLOW; XANTHAN GUM; FERRIC OXIDE RED; SODIUM HINOKITIOL; FERROSOFERRIC OXIDE; GLYCERYL STEARATE CITRATE; COCO-CAPRYLATE/CAPRATE

AussieZinc Mineral Sunscreen Vegan and Organic Extra Sensitive

WARNINGS

For external use only.

Do not use on damaged r broken skin.

When using this product keep out of eyes. Rinse with water to remove.
Stop use and ask a doctor if rash occurs.

Keep out of reach of children.

If product is swallowed, get medical help or contact a Poison Control Center right away.

Keep out of reach of children.

INACTIVE INGREDIENT

See ingredients on label